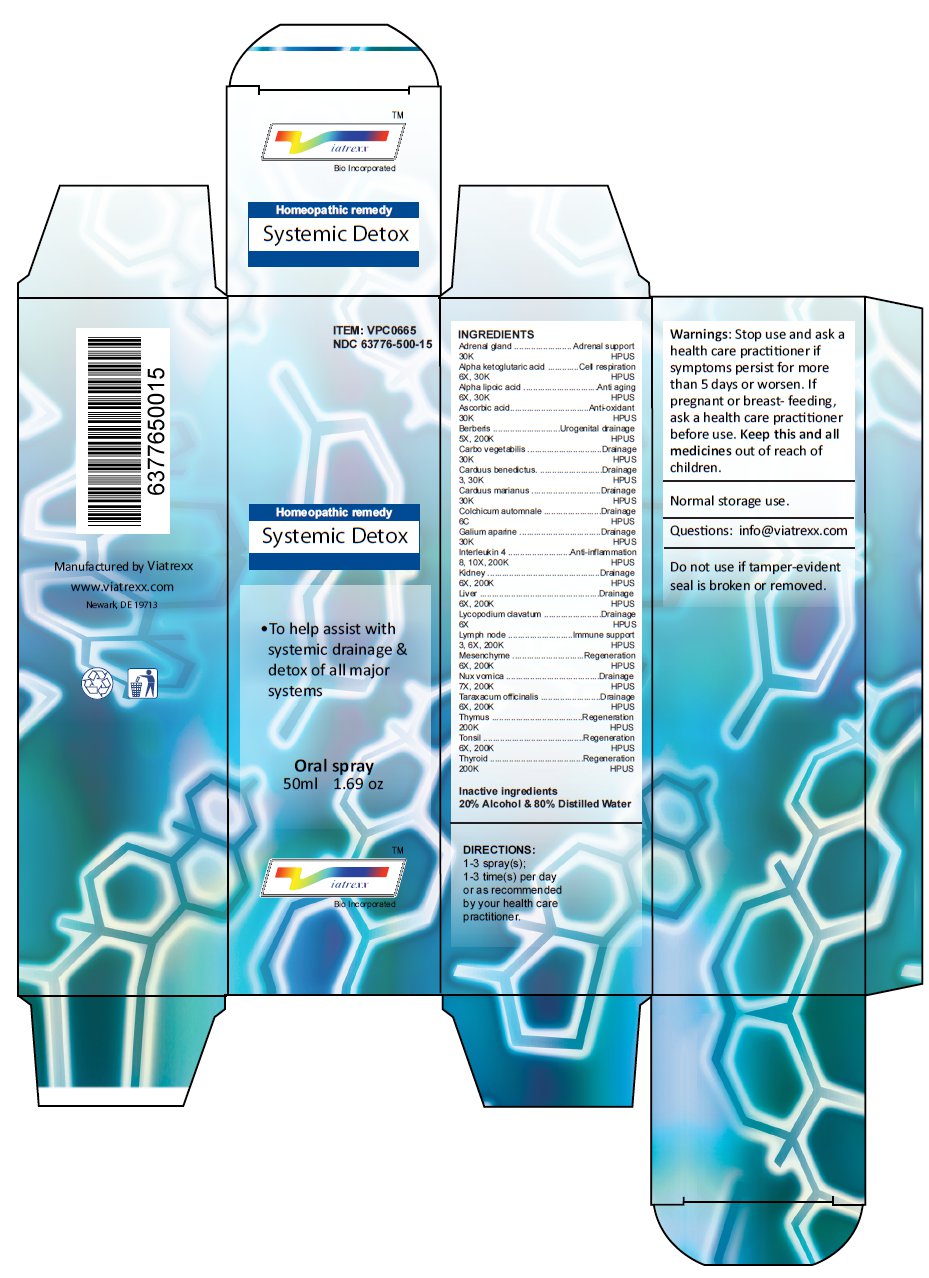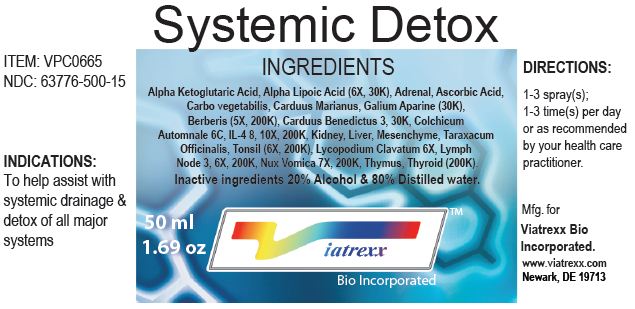 DRUG LABEL: Systemic Detox
NDC: 63776-500 | Form: SPRAY
Manufacturer: VIATREXX BIO INCORPORATED
Category: homeopathic | Type: HUMAN OTC DRUG LABEL
Date: 20221130

ACTIVE INGREDIENTS: BOS TAURUS ADRENAL GLAND 30 [kp_C]/1 mL; SUS SCROFA ADRENAL GLAND 30 [kp_C]/1 mL; .ALPHA.-KETOGLUTARIC ACID 30 [kp_C]/1 mL; .ALPHA.-LIPOIC ACID 30 [kp_C]/1 mL; ASCORBIC ACID 30 [kp_C]/1 mL; BERBERIS VULGARIS ROOT 200 [kp_C]/1 mL; ACTIVATED CHARCOAL 30 [kp_C]/1 mL; CENTAUREA BENEDICTA 30 [kp_C]/1 mL; MILK THISTLE 30 [kp_C]/1 mL; COLCHICUM AUTUMNALE BULB 6 [hp_C]/1 mL; GALIUM APARINE 30 [kp_C]/1 mL; BINETRAKIN 200 [kp_C]/1 mL; BEEF KIDNEY 200 [kp_C]/1 mL; PORK KIDNEY 200 [kp_C]/1 mL; BEEF LIVER 200 [kp_C]/1 mL; PORK LIVER 200 [kp_C]/1 mL; LYCOPODIUM CLAVATUM SPORE 6 [hp_X]/1 mL; BOS TAURUS LYMPH 200 [kp_C]/1 mL; SUS SCROFA LYMPH 200 [kp_C]/1 mL; BOS TAURUS MESENCHYME 200 [kp_C]/1 mL; SUS SCROFA MESENCHYME 200 [kp_C]/1 mL; STRYCHNOS NUX-VOMICA SEED 200 [kp_C]/1 mL; TARAXACUM OFFICINALE 200 [kp_C]/1 mL; BOS TAURUS THYMUS 200 [kp_C]/1 mL; SUS SCROFA THYMUS 200 [kp_C]/1 mL; BOS TAURUS TONSIL 200 [kp_C]/1 mL; SUS SCROFA TONSIL 200 [kp_C]/1 mL; THYROID, BOVINE 200 [kp_C]/1 mL; THYROID, PORCINE 200 [kp_C]/1 mL
INACTIVE INGREDIENTS: ALCOHOL; WATER

Systemic Detox

Active Ingredients

Adrenal gland 30K, Alpha ketoglutaric acid 6X 30K, Alpha lipoic acid 6X 30K, Ascorbic acid 30K, Berberis 5X 200K, Carbo vegetabilis 30K, Carduus benedictus 3 30K, Carduus marianus 30K, Colchicum automnale 6C, Galium aparine 30K, Interleukin 4 8 10X 200K, Kidney 6X 200K, Liver 6X 200K, Lycopodium clavatum 6X, Lymph node 3 6X 200K, Mesenchyme 6X 200K, Nux vomica 7X 200K, Taraxacum officinalis 6X 200K, Thymus 200K, Tonsil 6X 200K, Thyroid 200K

Purpose

Adrenal gland | Adrenal support
Alpha ketoglutaric acid | Cell respiration
Alpha lipoic acid | Anti aging
Ascorbic acid | Anti-oxidant
Berberis | Urogenital drainage
Carbo vegetabilis | Drainage
Carduus benedictus | Drainage
Carduus marianus | Drainage
Colchicum automnale | Drainage
Galium aparine | Drainage
Interleukin 4 | Anti-inflammation
Kidney | Drainage
Liver | Drainage
Lycopodium clavatum | Drainage
Lymph node | Immune support
Mesenchyme | Regeneration
Nux vomica | Drainage
Taraxacum officinalis | Drainage
Thymus | Regeneration
Tonsil | Regeneration
Thyroid | Regeneration

Uses

To help assist with systemic drainage & detox of all major systems

Warnings

Stop use and ask a health care practitioner if symptoms persist for more than 5 days or worsen. If pregnant or breast- feeding, ask a health care practitioner before use.

KEEP OUT OF REACH OF CHILDREN

Keep this and all medicines out of reach of children.

Directions

1-3 spray(s); 1-3 time(s) per day or as recommended by your health care practitioner.

Other Ingredients

Alcohol and Water

Other Information

Normal storage use.
Do not use if tamper-evident seal is broken or removed.

Questions

info@viatrexx.com

Principal Display Panel

ITEM: VPC0665
NDC 63776-500-15
Homeopathic remedy
Systemic Detox
• To help assist with systemic drainage & detox of all major systems
Oral spray
50ml 1.69 oz
Viatrexx™ Bio Incorporated
Manufactured by Viatrexx
www.viatrexx.com
Newark, DE 19713

Systemic Detox
50 mL
1.69 oz
Viatrexx™ Bio Incorporated
ITEM: VPC0665
NDC: 63776-500-15
INDICATIONS:
To help assist with systemic drainage & detox of all major systems
DIRECTIONS:
1-3 spray(s); 1-3 time(s) per day or as recommended by your health care practitioner.
Mfg. for
Viatrexx Bio Incorporated.
www.viatrexx.com
Newark, DE 19713